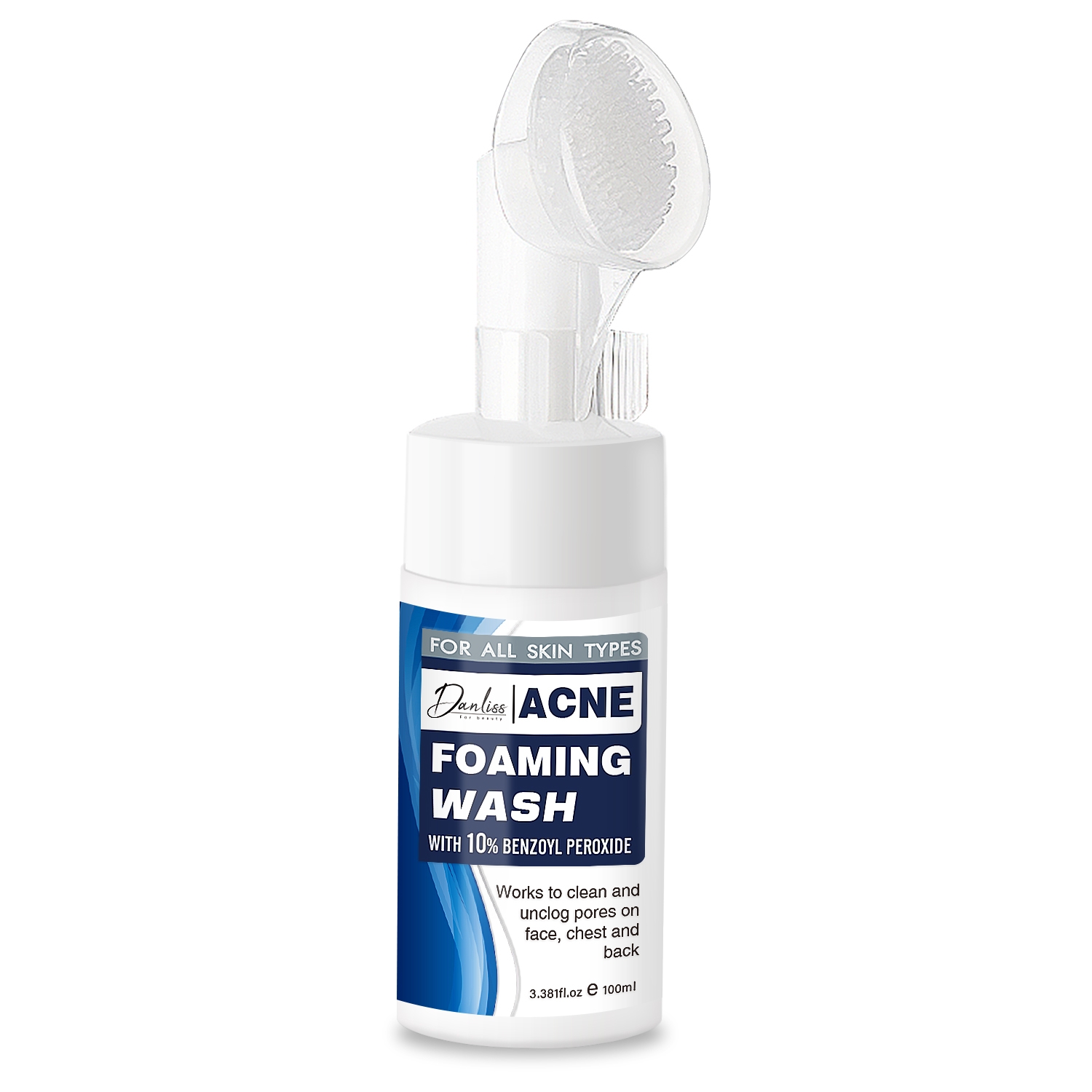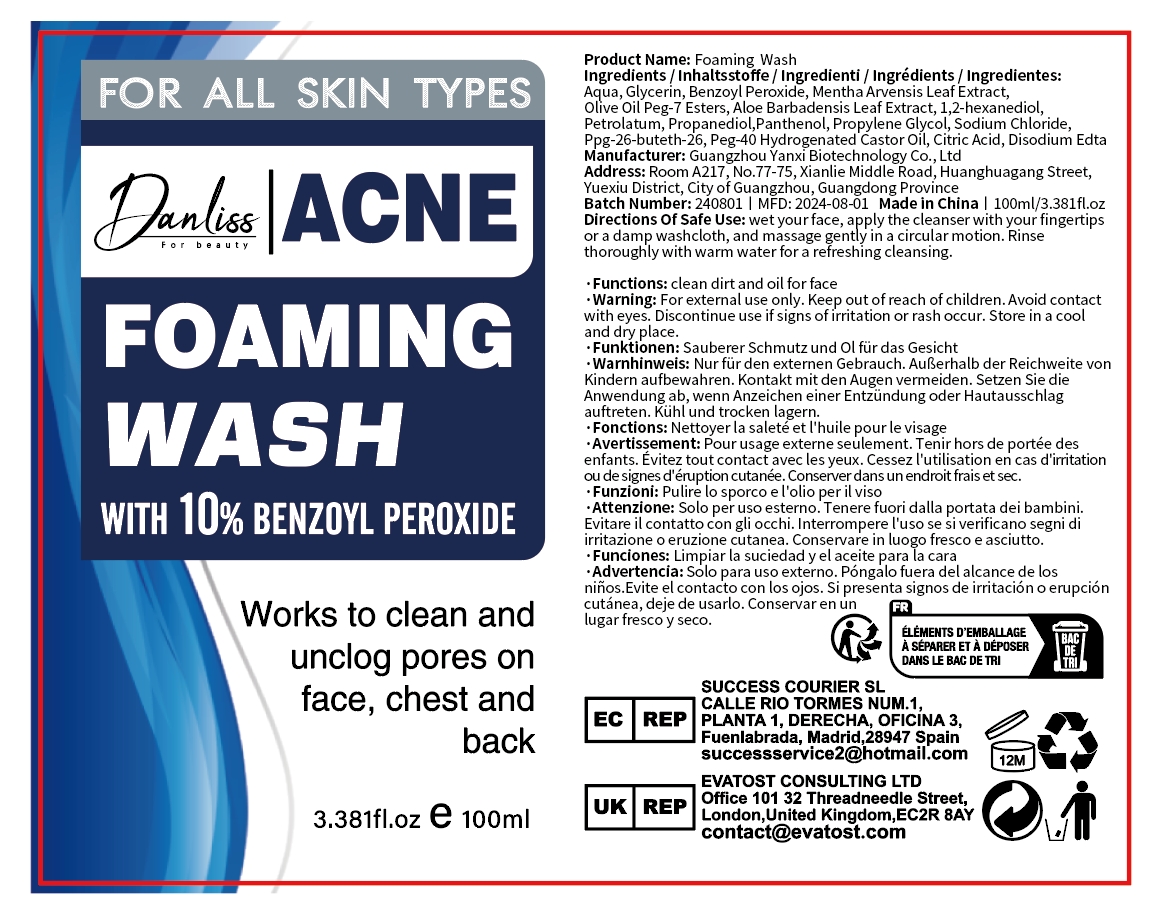 DRUG LABEL: Foaming Wash
NDC: 84025-250 | Form: CREAM
Manufacturer: Guangzhou Yanxi Biotechnology Co., Ltd
Category: otc | Type: HUMAN OTC DRUG LABEL
Date: 20241107

ACTIVE INGREDIENTS: 1,2-HEXANEDIOL 3 mg/100 mL; BENZOYL PEROXIDE 5 mg/100 mL
INACTIVE INGREDIENTS: WATER

DOSAGE AND ADMINISTRATION

wet you rface, apply the cleanser with your fingertips or a damp washcloth, and massage gently in a circular motion. Rinse thoroughly with warm water for a refreshing cleansing.

WARNINGS

Keep out of children

INACTIVE INGREDIENT

Aqua

INDICATIONS AND USAGE

For daily skin care

Keep out of children

PURPOSE

Clean dirt and oil for face